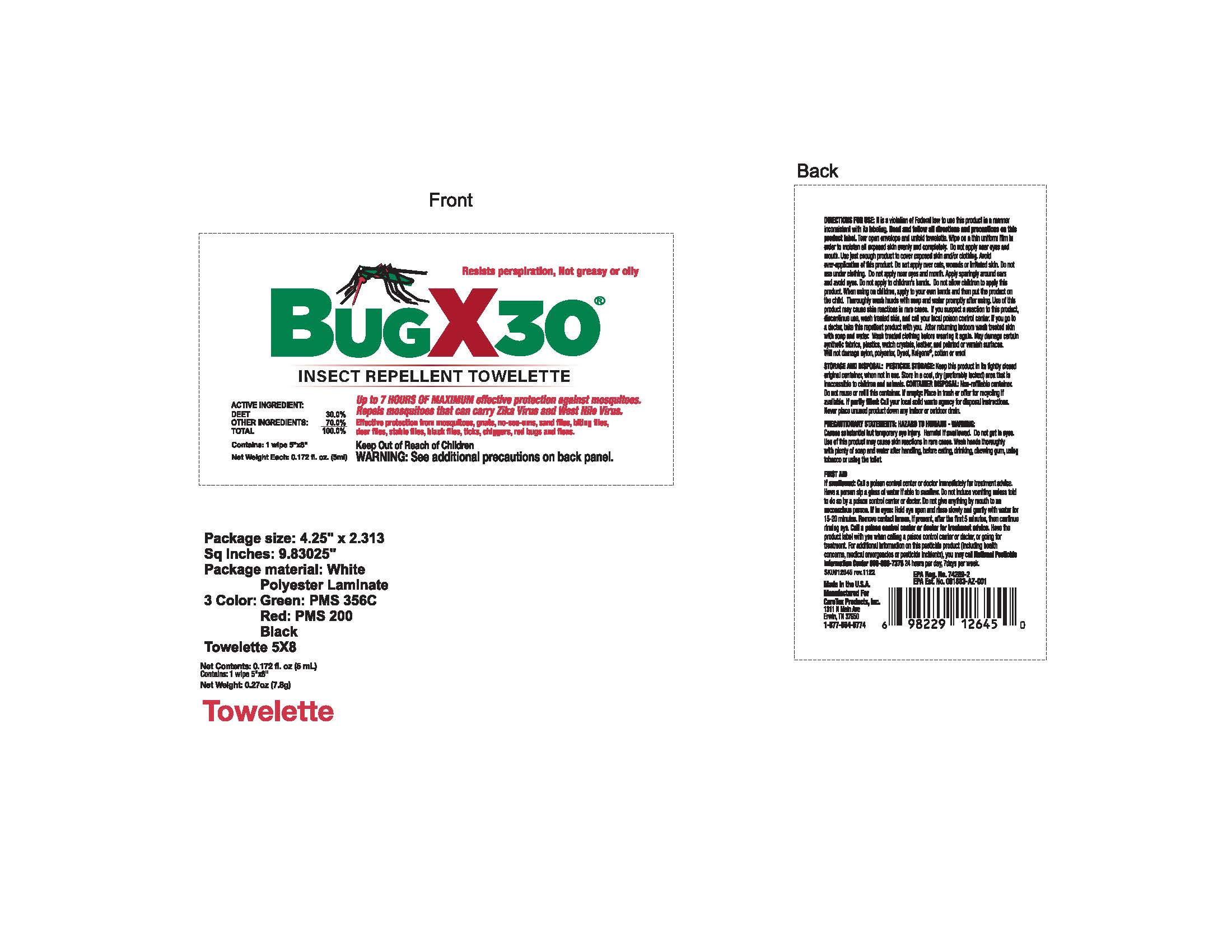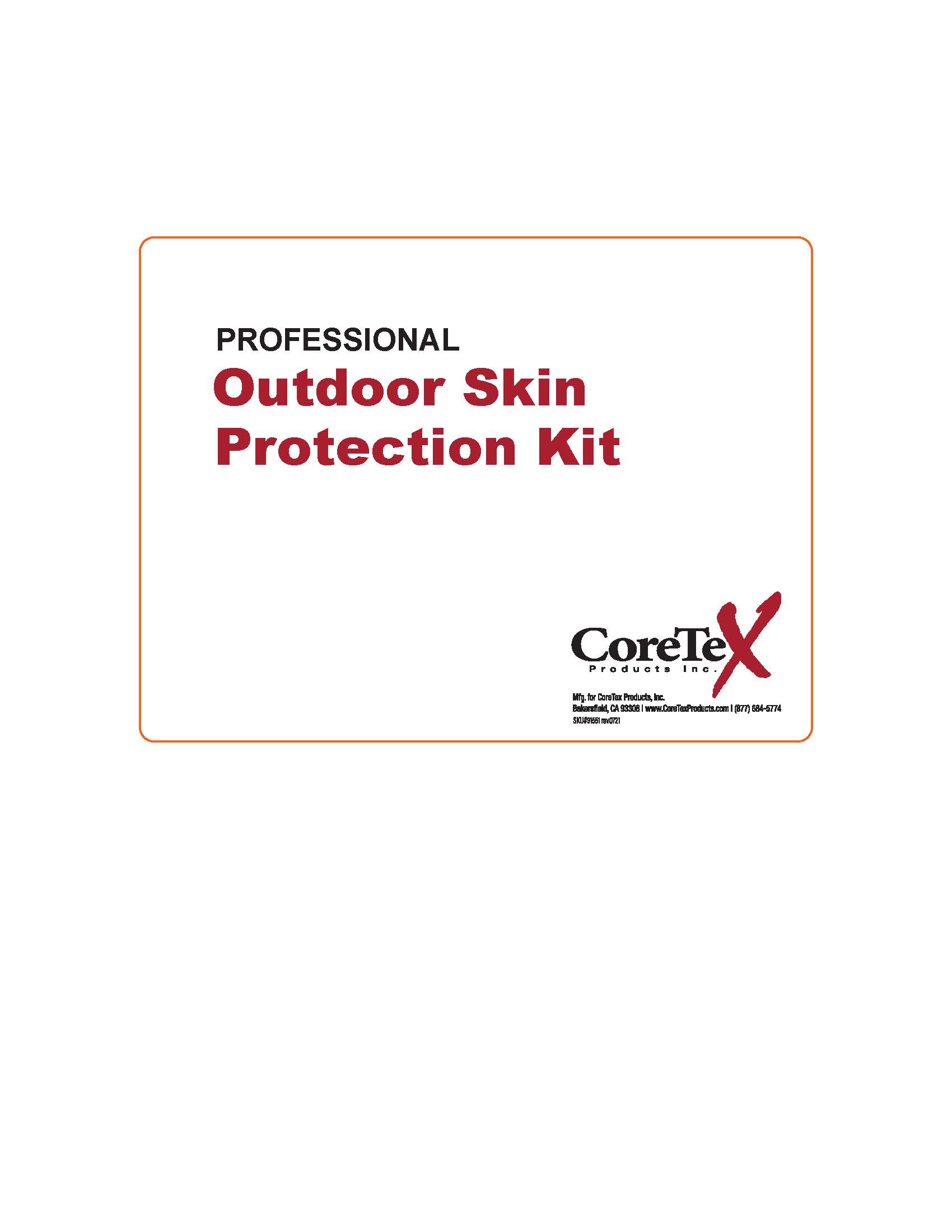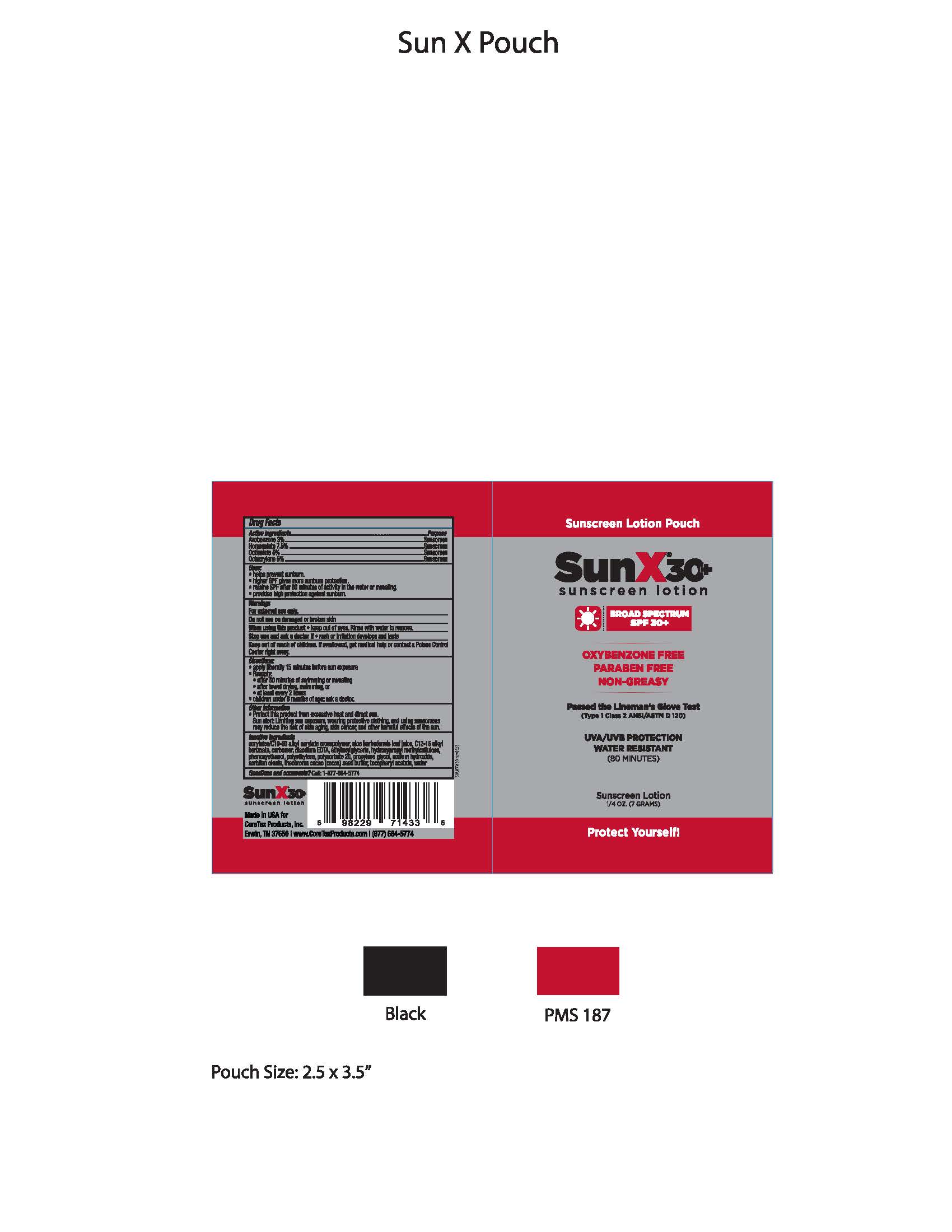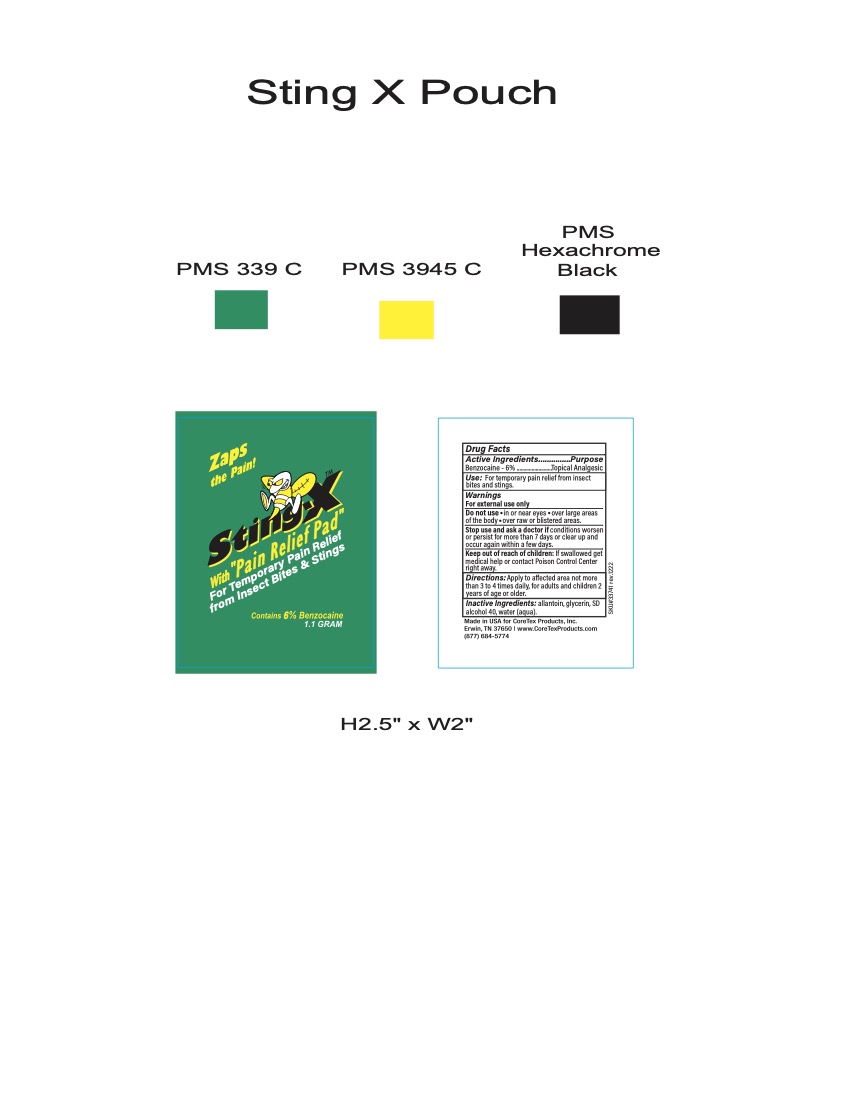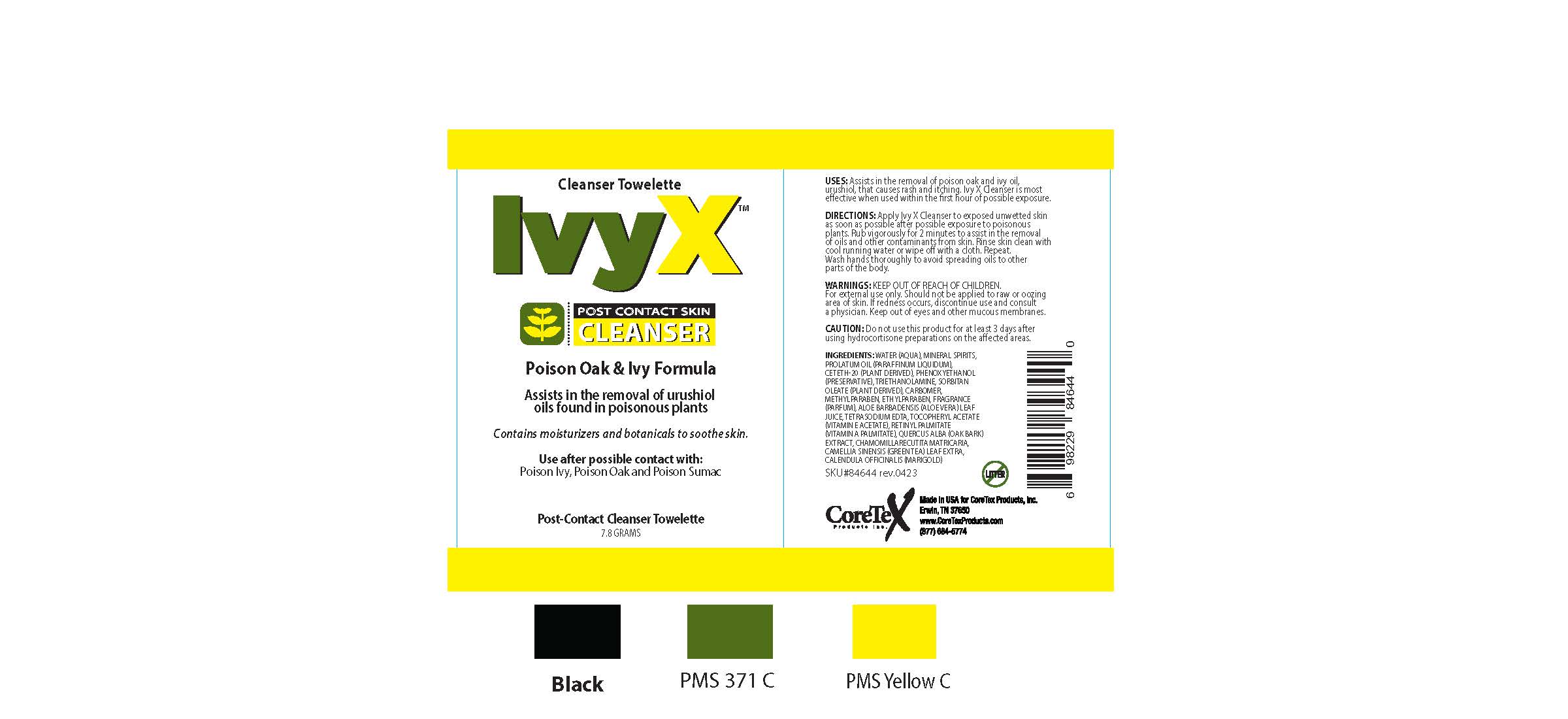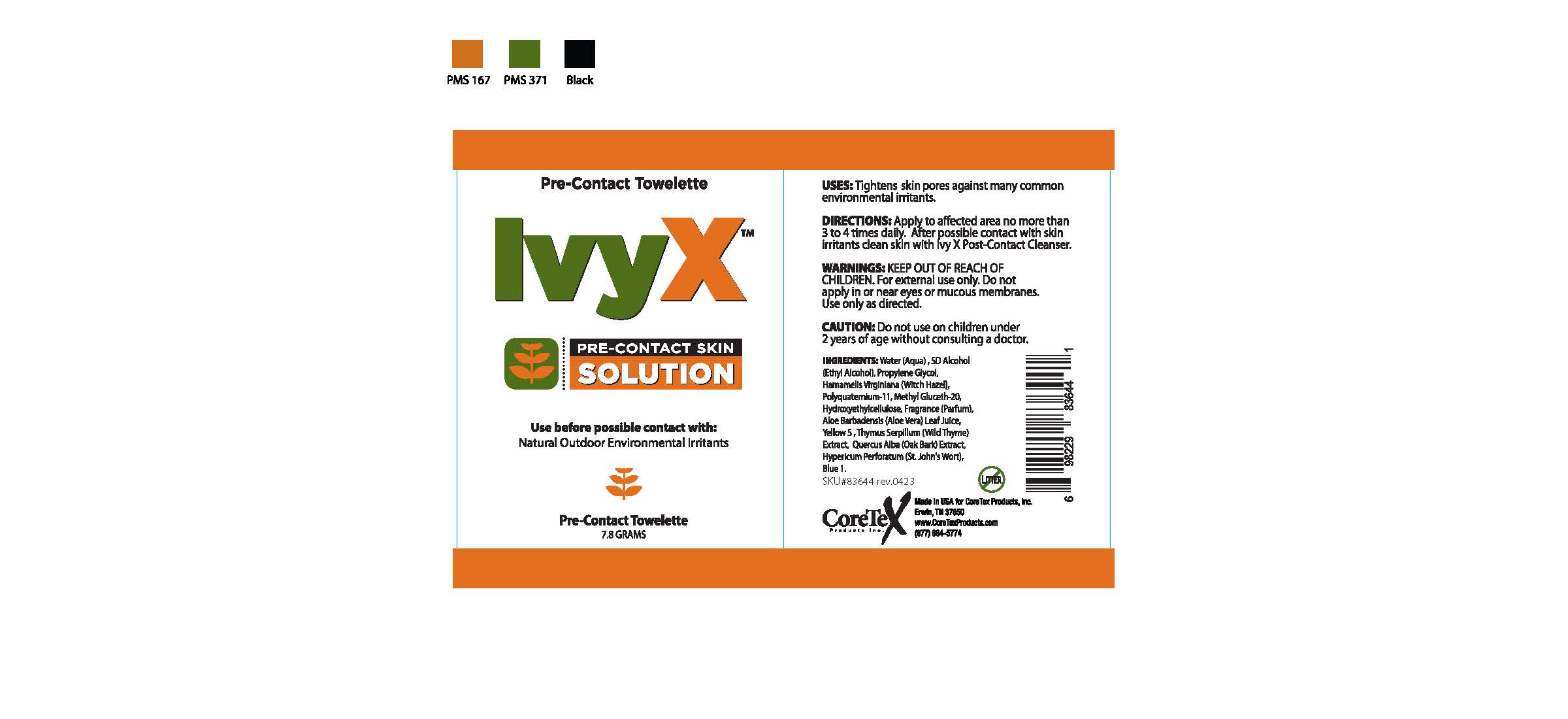 DRUG LABEL: CoreTex Professional Outdoor Skin Protection Wallet Refill
NDC: 65753-513 | Form: KIT | Route: TOPICAL
Manufacturer: CoreTex Products Inc
Category: otc | Type: HUMAN OTC DRUG LABEL
Date: 20231120

ACTIVE INGREDIENTS: HOMOSALATE 7.5 g/100 mL; OCTISALATE 5 g/100 mL; AVOBENZONE 3 g/100 mL; OCTOCRYLENE 5 g/100 mL; BENZOCAINE 6 g/100 mL
INACTIVE INGREDIENTS: MEDIUM DENSITY POLYETHYLENE; DISODIUM EDTA-COPPER; THEOBROMA CACAO WHOLE; ETHYLHEXYLGLYCERIN; POLYSORBATE 20; METHYLCELLULOSE, UNSPECIFIED; SODIUM HYDROXIDE; ACRYLATES CROSSPOLYMER-6; ALKYL (C12-15) BENZOATE; CARBOMER HOMOPOLYMER, UNSPECIFIED TYPE; .ALPHA.-TOCOPHEROL ACETATE; ALOE VERA LEAF; WATER; PHENOXYETHANOL; PEG-6 SORBITAN OLEATE; PROPYLENE GLYCOL PROPYL ETHER; WATER; ALLANTOIN; GLYCERIN; ALCOHOL

CoreTex Professional Outdoor Skin Protection Hardcase
65753-513

SunX 30 Active Ingredients:

Avobenzone 3.0%

Homosalate 7.5%

Octisalate 5.0%

Octocrylene 5.0%

SunX 30 Purpose

Sunscreen

Sunscreen

Sunscreen

Sunscreen

SunX 30 Uses:

- helps prevent sunburn.
- higher SPF gives more sunburn protection.
- retains SPF after 80 minutes of activity in the water or sweating.
- provides high protection against sunburn.

SunX 30 Warnings

For external use only

SunX 30 Do Not Use

- on damaged or broken skin

When using this product

- keep out of the eyes
- rinse with water to remove

Stop use and ask a doctor if

- rash or irritation develops and lasts

Keep out of reach of children.

If swallowed, get medical help or contact Poison Control Center right away.

SunX 30 Directions:

- apply liberally and evenly 15 minutes before sun exposure
- reapply:
- after 80 minutes of swimming or sweating
- after towel drying, swimming, or
- at least every 2 hours
- children under 6 months of age: Ask a doctor

SunX 30 Other Information:

- protect this product from excessive heat or direct sun.

Sun alert: Limiting sun exposure, wearing protective clothing, and using sunscreens may reduce the risk of skin aging, skin cancer, and other harmful effects of the sun.

SunX 30 Inactive Ingredients:

acrylates/C10-30 alkyl acrylate crosspolymer, aloe barbadensis leaf juice, C12-15 alkyl benzoate, carbomer, disodium EDTA, ethylexyiglycerin, hydroxypropyl methylcellulose, phenoxyethanol, polyethylene, polysorbate 20, propylene glycol, sodium hydroxide, sorbitan oleate, theobroma cacao (cocoa) seed butter, tocopheryl acetate, water

SunX 30 Questions?

Call: 1-877-684-5774

Sting X Active Ingredients:

Benzocaine 6%

Sting X Purpose

Topical Analgesic

Sting X Use:

For temporary pain relief from insect bites and stings

Sting X Warnings

For external use only

Do not use

- in or near eyes
- over large areas of the body
- over raw or blistered areas

Stop use and ask a doctor if

- conditions worsen or persist for more than 7 days or clear up and occur again within a few days

Keep out of reach of children.

If swallowed get medical help or contact Poison Control center right away.

Sting X Directions:

Apply to affected area not more than 3 to 4 times daily, for adults and children 2 years of age or older.

Sting X Inactive Ingredients:

allantoin, glycerin, SD alcohol 40, water (aqua)

Sting X Other Information:

Made in USA for CoreTex Products, Inc.

Erwin, TN 37650

www.CoreTexProducts.com (877)684-5774